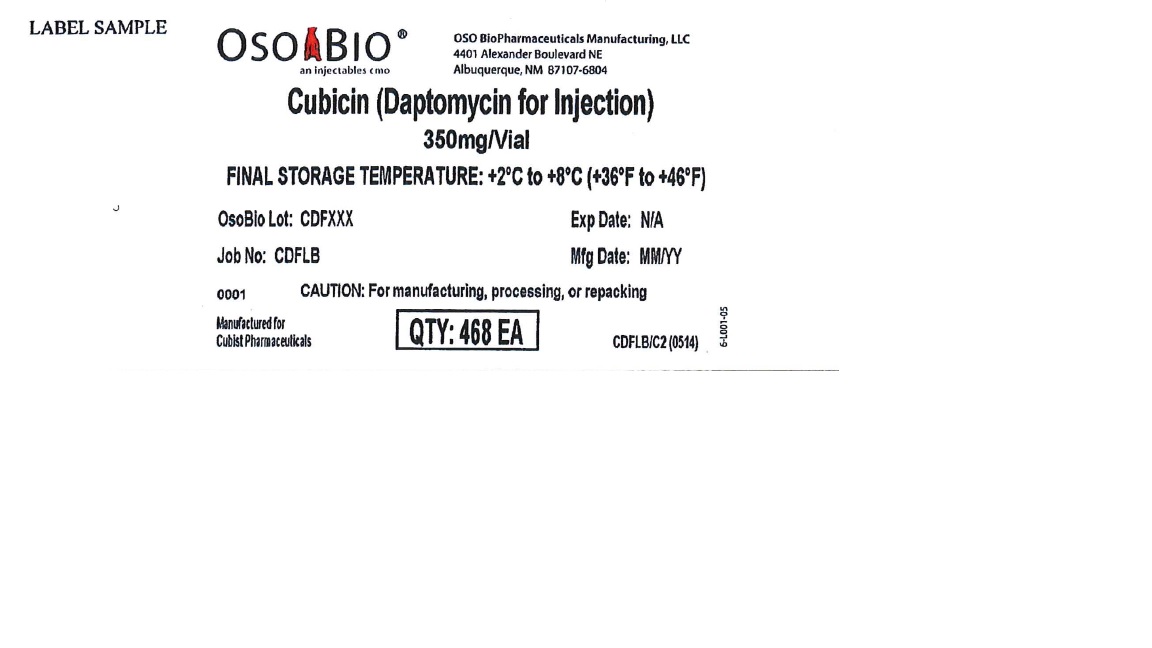 DRUG LABEL: Cubicin
NDC: 70835-1001 | Form: INJECTION
Manufacturer: Curia New Mexico, LLC
Category: prescription | Type: HUMAN PRESCRIPTION DRUG LABEL
Date: 20241014

ACTIVE INGREDIENTS: DAPTOMYCIN 350 mg/350 mg

Cubicin - Drug Listing for CDF Product Code